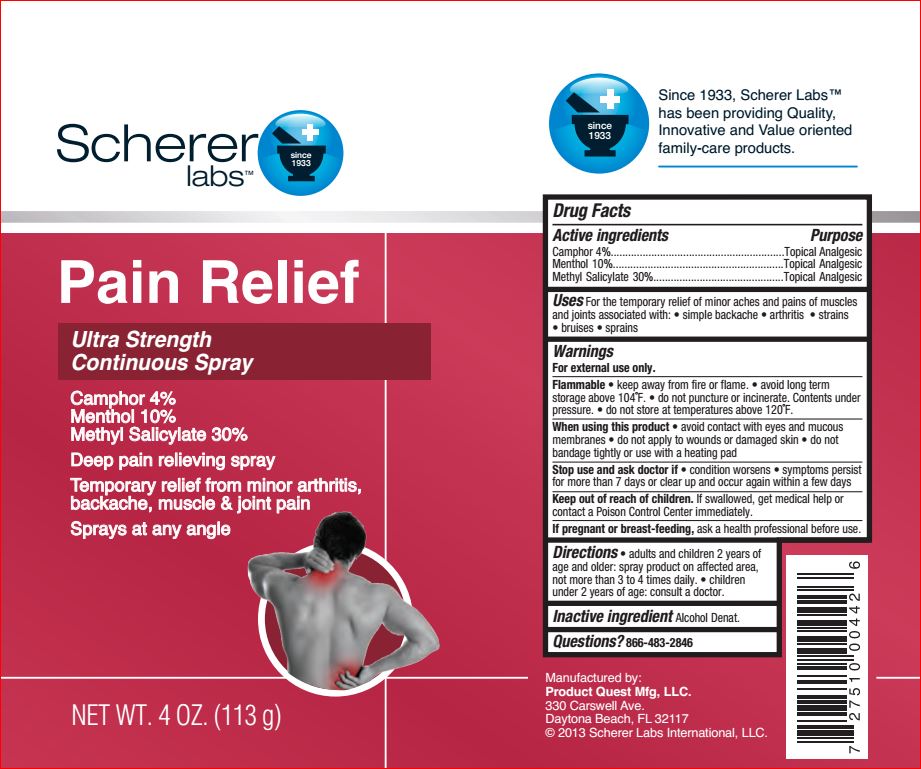 DRUG LABEL: Ultra Strength Pain Relief
NDC: 64048-5114 | Form: SPRAY
Manufacturer: Product Quest Mfg
Category: otc | Type: HUMAN OTC DRUG LABEL
Date: 20180625

ACTIVE INGREDIENTS: CAMPHOR (SYNTHETIC) 4 g/100 g; Menthol 10 g/100 g; Methyl Salicylate 30 g/100 g
INACTIVE INGREDIENTS: ALCOHOL

Drug Facts

Active ingredients Purpose

Camphor – 4.00% Topical Analgesic
Menthol – 10.00% Topical Analgesic
Methyl Salicylate – 30.00% Topical Analgesic

Uses

- temporarily relieves minor pain associated with:
- arthritis
- simple backache
- muscle strains
- bruises
- muscle sprains

Warnings

For external use only

Flammable

• keep away from fire or flame. • avoid long term
storage above 104˚F. • do not puncture or incinerate. Contents under
pressure. • do not store at temperatures above 120˚F

• do not use while smoking or near heat or flame
• avoid long term storage above 104F
• do not puncture or incinerate. Contents under pressure
• do not store at temperature above 120F

When using this product

• avoid contact with eyes and mucous membranes
• do not apply to wounds or damages skin
• do not bandage tightly or use with a heating pad
• use only as directed

Stop use and ask a doctor if

• condition worsens
• symptoms last more than 7 days or clear up and occur again within a few days

Keep out of reach of the children

If swallowed, get medical help or contact a Poison Control Center right away

Directions

• shake well
• adults and children 2 years of age and older: spray on affected area, not more than 3 to 4 times daily
• children under 2 years of age: consult a doctor

Inactive ingredients

Alcohol Denat.